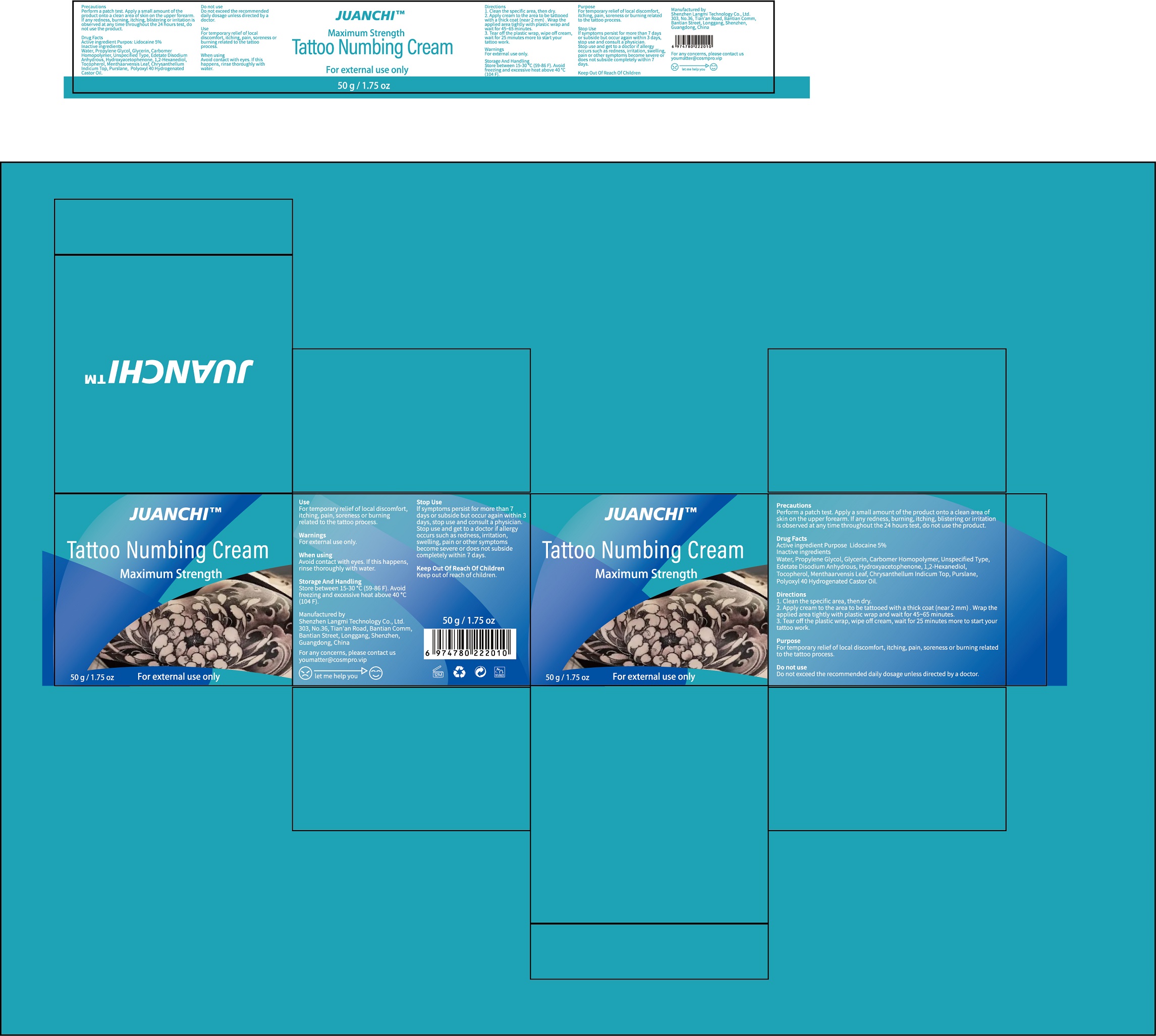 DRUG LABEL: JUANCHI Tattoo Numbing
NDC: 83603-001 | Form: CREAM
Manufacturer: Shenzhen Langmi Technology Co., Ltd.
Category: otc | Type: HUMAN OTC DRUG LABEL
Date: 20230806

ACTIVE INGREDIENTS: LIDOCAINE 5 g/100 g
INACTIVE INGREDIENTS: WATER; PROPYLENE GLYCOL; GLYCERIN; CARBOMER HOMOPOLYMER, UNSPECIFIED TYPE; EDETATE DISODIUM ANHYDROUS; HYDROXYACETOPHENONE; 1,2-HEXANEDIOL; TOCOPHEROL; MENTHA ARVENSIS LEAF; CHRYSANTHELLUM INDICUM TOP; PURSLANE; POLYOXYL 40 HYDROGENATED CASTOR OIL

Active Ingredient(s)

Lidocaine 5%

Purpose

For temporary relief of local discomfort, itching,pain, soreness or burning related to the tattooprocess.

Use

For temporary relief of local discomfort, itching, pain,soreness or burning related to the tattoo process.

Warnings

For external use only.

Do not use

Do not exceed the recommended daily dosage unless directed by a doctor.

WHEN USING

Avoid contact with eyes. If this happens, rinse thoroughly with water.

STOP USE

lf symptoms persist for more than 7 days or subside but occur again within 3 days, stop use and consult a physician.
Stop use and get to a doctor if allergy occurs such as redness, irritation, swelling, pain or other symptoms become severe or does not subside completely within 7 days.

Keep out of reach of children.

Directions

1. Clean the specific area, thendry.
2.Apply cream to the area to betattooed with a thick coat (near 2mm) . Wrap the applied area tightly with plasticwrap and waitfor 45~65 minutes.
3.Tear off the plastic wrap, wipeoff cream, wait for 25 minutesmore to start your tattoo work.

Storage and handling

- Store between 15-30℃(59-86F).Avoid freezing and excessive heat above 40℃(104F).

Inactive ingredients

WATER,PROPYLENE GLYCOL,GLYCERIN,CARBOMER HOMOPOLYMER, UNSPECIFIED TYPE,EDETATE DISODIUM ANHYDROUS,
HYDROXYACETOPHENONE,1,2-HEXANEDIOL,Tocopherol,MENTHAARVENSIS LEAF,CHRYSANTHELLUM INDICUM TOP, PURSLANE,POLYOXYL40 HYDROGENATED CASTOR OIL